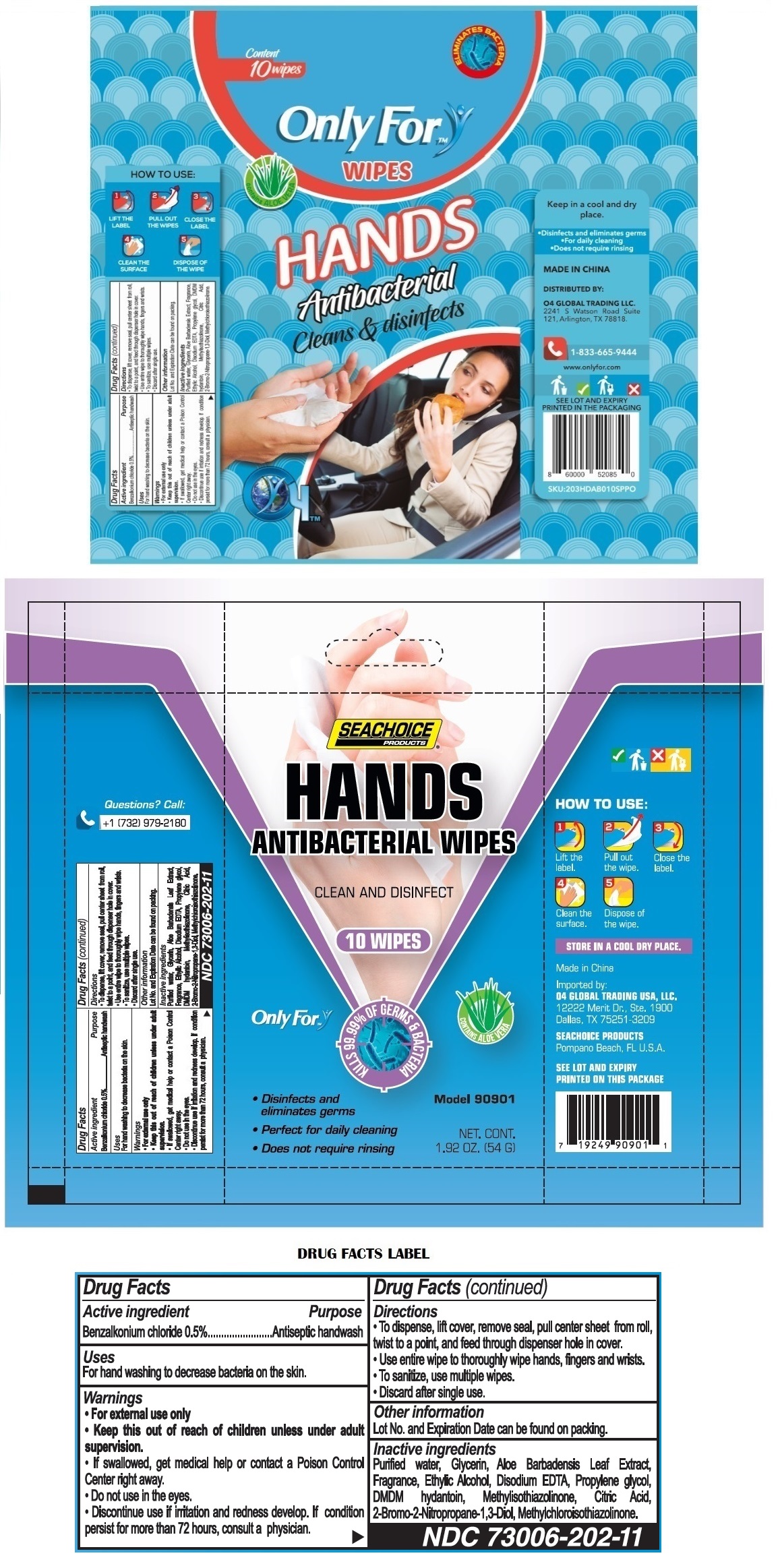 DRUG LABEL: Only For - Wipes
NDC: 73006-202 | Form: CLOTH
Manufacturer: O4 Global Trading Usa, Llc
Category: otc | Type: HUMAN OTC DRUG LABEL
Date: 20211013

ACTIVE INGREDIENTS: BENZALKONIUM CHLORIDE 0.05 mg/1 1
INACTIVE INGREDIENTS: WATER; GLYCERIN; ALOE VERA LEAF; ALCOHOL; EDETATE DISODIUM ANHYDROUS; PROPYLENE GLYCOL; DMDM HYDANTOIN; METHYLISOTHIAZOLINONE; CITRIC ACID MONOHYDRATE; BRONOPOL ; METHYLCHLOROISOTHIAZOLINONE

Only For - Wipes

Active ingredient

Benzalkonium chloride 0.5%

Purpose

Antiseptic handwash

Uses

For hand washing to decrease bacteria on the skin.

Warnings

• For external use only

• Do not use in the eyes.

• Discontinue use if irritation and redness develop. If condition persist for more than 72 hours, consult a physician.

KEEP OUT OF REACH OF CHILDREN

• Keep this out of reach of children unless under adult supervision.

• If swallowed, get medical help or contact a Poison Control Center right away.

Directions

• To dispense, lift cover, remove seal, pull center sheet from roll, twist to a point, and feed through dispenser hole in cover.

• Use entire wipe to thoroughly wipe hands, fingers and wrists.

• To sanitize, use multiple wipes.

• Discard after single use.

Other information

Lot No. and Expiration Date can be found on packing.

Inactive ingredients

Purified water, Glycerin, Aloe Barbadensis Leaf Extract, Fragrance, Ethylic Alcohol, Disodium EDTA, Propylene glycol, DMDM hydantoin, Methylisothiazolinone, Citric Acid, 2-Bromo-2-Nitropropane-1,3-Diol, Methylchloroisothiazolinone.

SEACHOICE PRODUCTS®

HANDS ANTIBACTERIAL WIPES

CLEAN AND DISINFECT

KILLS 99.99% OF GERMS & BACTERIA

CONTAINS ALOE VERA

• Disinfects and eliminates germs

• Perfect for daily cleaning

• Does not require rinsing

Questions? Call: +1 (732) 979-2180

HOW TO USE:

1 Lift the label.

2 Pull out the wipe.

3 Close the label.

4 Clean the surface.

5 Dispose of the wipe.

STORE IN A COOL DRY PLACE.

Made in China

Imported by:

O4 GLOBAL TRADING USA, LLC.
12222 Merit Dr., Ste. 1900
Dallas, TX 75251-3209

SEACHOICE PRODUCTS
Pompano Beach, FL U.S.A.

SEE LOT AND EXPIRY PRINTED ON THIS PACKAGE